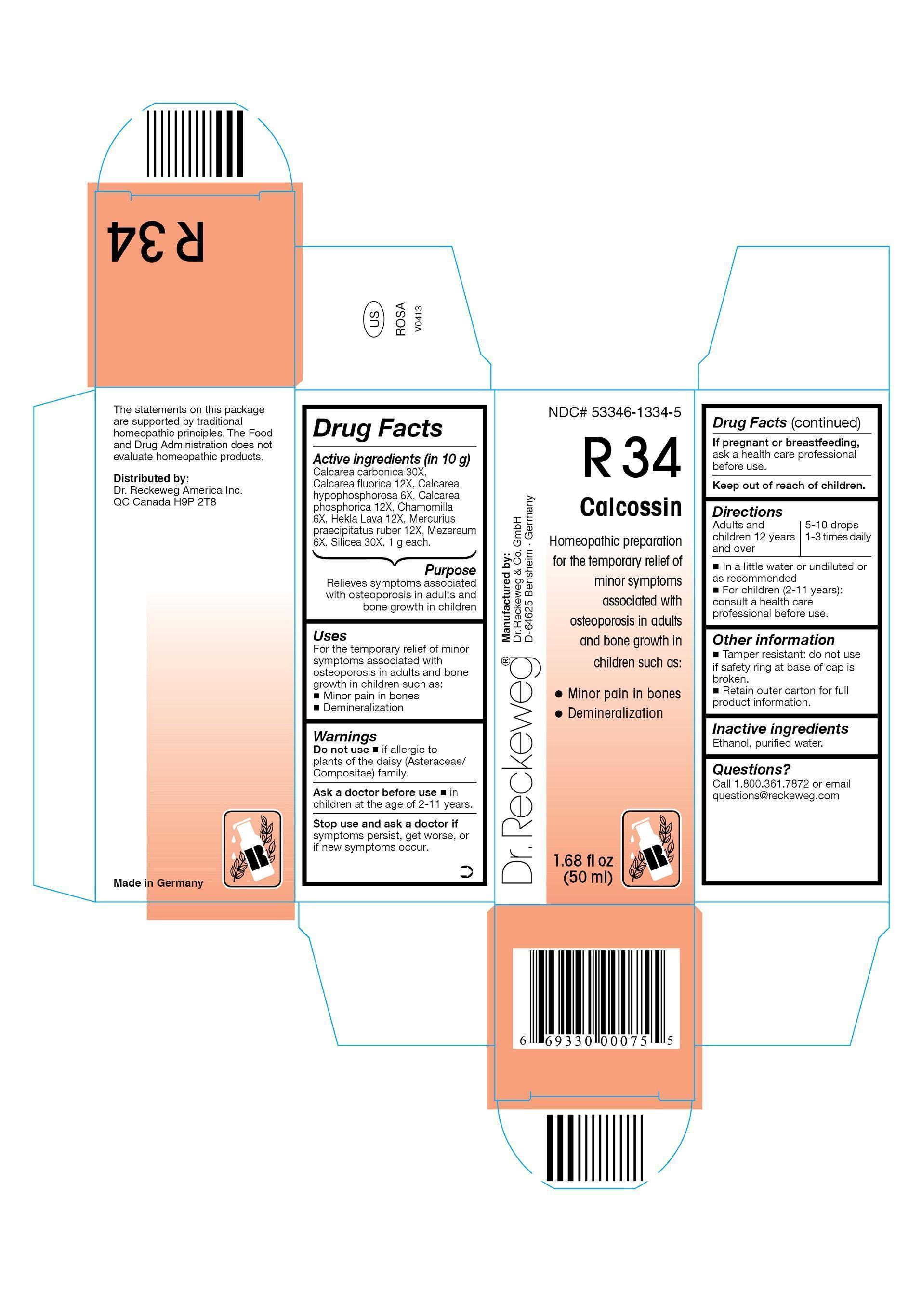 DRUG LABEL: DR. RECKEWEG R34 Calcossin
NDC: 53346-1334 | Form: LIQUID
Manufacturer: PHARMAZEUTISCHE FABRIK DR. RECKEWEG & CO
Category: homeopathic | Type: HUMAN OTC DRUG LABEL
Date: 20130404

ACTIVE INGREDIENTS: OYSTER SHELL CALCIUM CARBONATE, CRUDE 30 [hp_X]/50 mL; CALCIUM FLUORIDE 12 [hp_X]/50 mL; CALCIUM HYPOPHOSPHITE 6 [hp_X]/50 mL; CALCIUM PHOSPHATE, DIBASIC, DIHYDRATE 12 [hp_X]/50 mL; MATRICARIA RECUTITA 6 [hp_X]/50 mL; HEKLA LAVA 12 [hp_X]/50 mL; MERCURIC OXIDE 12 [hp_X]/50 mL; DAPHNE MEZEREUM BARK 6 [hp_X]/50 mL; SILICON DIOXIDE 30 [hp_X]/50 mL
INACTIVE INGREDIENTS: ALCOHOL; WATER

DR. RECKEWEG R34 Calcossin

Active ingredients

Calcarea carbonica 30X, Calcarea fluorica 12X, Calcarea hypophosphorosa 6X, Calcarea phosphorica 12X, Chamomilla 6X, Hekla Lava 12X, Mercurius praecipitatus ruber 12X, Mezereum 6X, Silicea 30X,

1 g each in 10 g.

Purpose

Relieves symptoms associated with osteoporosis in adults and bone growth in children

Uses

For the temporary relief of minor symptoms associated with osteoporosis in adults and bone growth in children such as:

- Minor pain in bones
- Demineralization

Warnings

Do not use

- if allergic to plants of the daisy (Asteraceae/Compositae) family.

Ask a doctor before use

- in children at the age of 2-11 years.

Stop use and ask a doctor if symptoms persist, get worse, or if new symptoms occur.

PREGNANCY OR BREAST FEEDING

If pregnant or breastfeeding, ask a health care professional before use.

Keep out of reach of children.

Directions
Adults and children ≥ 12 years 5-10 drops 1-3 times daily in a little water or undiluted or as recommended. For children (2-11 years): consult a health care professional before use.

Other information

- Tamper resistant: do not use if safety ring at base of cap is broken.
- Retain outer carton for full product information.

Inactive ingredients
Ethanol, purified water.

Questions?
Call 1.800.361.7872 or email questions@reckeweg.com

PACKAGE LABEL

NDC# 53346-1334-5
Dr. Reckeweg R34 Calcossin
Homeopathic preparation for the temporary relief of minor symptoms associated with osteoporosis and bone growth in children such as:

- Minor pain in bones
- Demineralization

Manufactured by:
Dr. Reckeweg Co. GmbH
D-64625 Bensheim
Germany
1.68 fl oz
(50 ml)